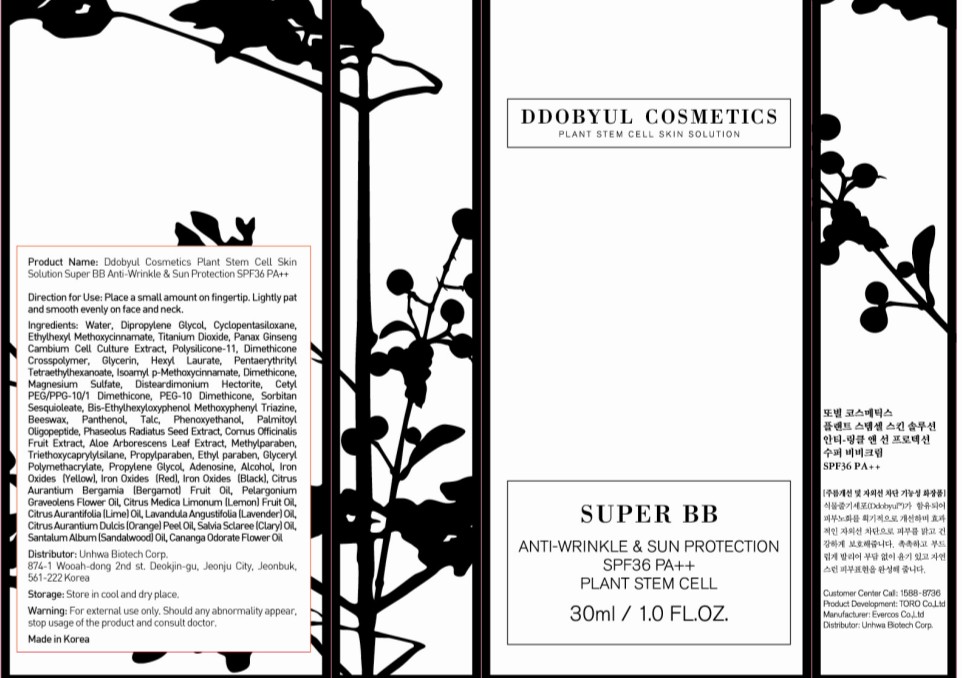 DRUG LABEL: SUPER BB
NDC: 50556-001 | Form: CREAM
Manufacturer: UNHWA CORPORATION
Category: otc | Type: HUMAN OTC DRUG LABEL
Date: 20100520

ACTIVE INGREDIENTS: TITANIUM DIOXIDE 1.6 mL/30 mL

Drug Facts

Active Ingredient: TITANIUM DIOXIDE

Inactive Ingredients:
Water, Dipropylene Glycol, Cyclopentasiloxane, Ethylhexyl Methoxycinnamate, Panax Ginseng Cambium Cell Culture Extract, Polysilicone-11, Dimethicone Crosspolymer, Glycerin, Hexyl Laurate, Pentaerythrityl Tetraethylhexanoate, Isoamyl p-Methoxycinnamate, Dimethicone, Magnesium Sulfate, Disteardimonium Hectorite, Cetyl PEG/PPG-10/1 Dimethicone, PEG-10 Dimethicone, Sorbitan Sesquioleate, Bis-Ethylhexyloxyphenol Methoxyphenyl Triazine, Beeswax, Panthenol, Talc, Phenoxyethanol, Palmitoyl Oligopeptide, Phaseolus Radiatus Seed Extract, Cornus Officinalis Fruit Extract, Aloe Arborescens Leaf Extract, Methylparaben, Triethoxycaprylylsilane, Propylparaben, Ethyl paraben, Glyceryl Polymethacrylate, Propylene Glycol, Adenosine, Alcohol, Iron Oxides(Yellow), Iron Oxides(Red), Iron Oxides(Black), Fragrance

DESCRIPTION

Direction for Use: Place a small amount on fingertip. Lightly pat and smooth evenly on face and neck.
Storage: Store in cool and dry place.
Warning: For external use only. Should any abnormality appear, stop usage of the product and consult doctor.